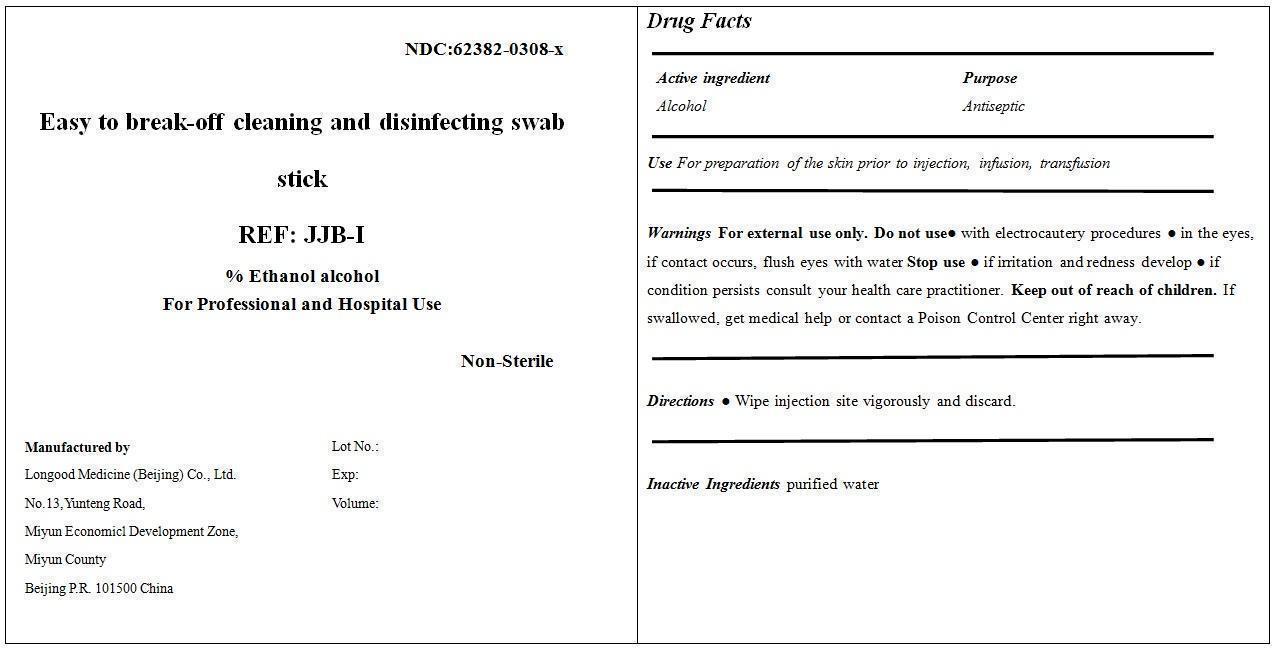 DRUG LABEL: Easy to break-off cleaning and disinfecting swabstick JJB-I
NDC: 62382-0308 | Form: SWAB
Manufacturer: Longood Medicine (Beijing) Co., Ltd.
Category: otc | Type: HUMAN OTC DRUG LABEL
Date: 20200106

ACTIVE INGREDIENTS: ALCOHOL 0.7 mL/1 mL
INACTIVE INGREDIENTS: WATER 0.3 mL/1 mL

Drug Fact

Active Ingredient

Alcohol 70%

Purpose

Antiseptic

Use

For preparation of the skin prior to injection, infusion, transfusion

Dosage

Swab

Warnings

For external use only

Do Not Use

● with electrocautery procedures

● in the eyes, if contact occurs, flush eyes with water

Stop Use

● if irritation and redness develop

● if condition persists consult your health care practitioner.

Keep Out of Reach of Children

If swallowed, get medical help or contact a Poison Control Center right away.

Directions

Wipe injection site vigorously and discard.

Inactive Ingredient

Purified Water